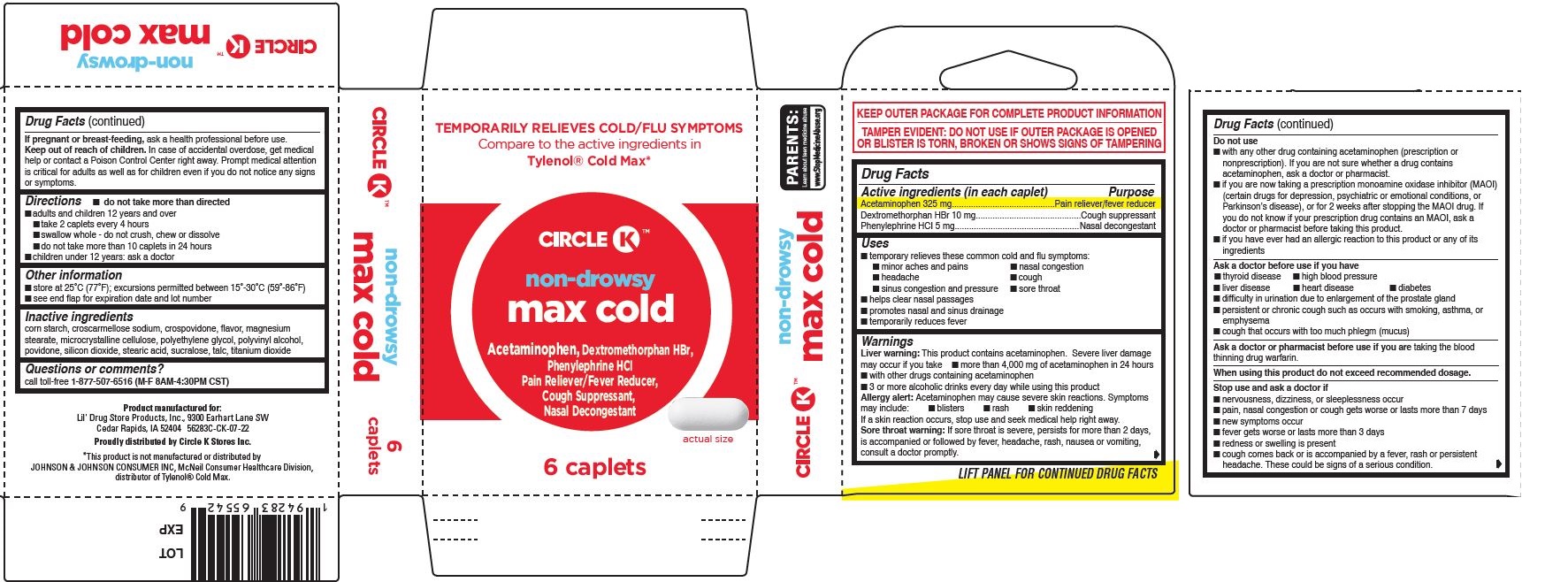 DRUG LABEL: Non-Drowsy Max Cold
NDC: 66715-5628 | Form: TABLET, FILM COATED
Manufacturer: Lil' Drug Store Products, Inc.
Category: otc | Type: HUMAN OTC DRUG LABEL
Date: 20231214

ACTIVE INGREDIENTS: DEXTROMETHORPHAN HYDROBROMIDE 10 mg/1 1; ACETAMINOPHEN 325 mg/1 1; PHENYLEPHRINE HYDROCHLORIDE 5 mg/1 1
INACTIVE INGREDIENTS: POVIDONE, UNSPECIFIED; SUCRALOSE; TALC; STEARIC ACID; POLYETHYLENE GLYCOL, UNSPECIFIED; POLYVINYL ALCOHOL, UNSPECIFIED; SILICON DIOXIDE; TITANIUM DIOXIDE; CROSCARMELLOSE SODIUM; MAGNESIUM STEARATE; CELLULOSE, MICROCRYSTALLINE; STARCH, CORN; CROSPOVIDONE

Non-Drowsy Max Cold, Circle K™

Active ingredients

Active ingredients (in each caplet)

Acetaminophen 325 mg
Dextromethorphan HBr 10 mg
Phenylephrine HCI 5 mg

Purpose

Pain reliever/fever reducer
Cough suppressant
Nasal decongestant

Uses

- temporary relieves these common cold and flu symptoms:
- minor aches and pains
- nasal congestion
- headache
- cough
- sinus congestion and pressure
- sore throat
- helps clear nasal passages
- promotes nasal and sinus drainage
- temporarily reduces fever

Warnings

Liver warning

Liver warning: This product contains acetaminophen. Severe liver damage may occur if you take

- more than 4,000 mg of acetaminophen in 24 hours
- with other drugs containing acetaminophen
- 3 or more alcoholic drinks every day while using this product

Allergy alert

Allergy alert: Acetaminophen may cause severe skin reactions. Symptoms may include:

- blisters
- rash
- skin reddening

If a skin reaction occurs, stop use and seek medical help right away. Sore throat warning: If sore throat is severe, persists for more than 2 days, is accompanied or followed by fever, headache, rash, nausea or vomiting, consult a doctor promptly.

Do not use

- with any other drug containing acetaminophen (prescription or nonprescription). If you are not sure whether a drug contains acetaminophen, ask a doctor or pharmacist.
- if you are now taking a prescription monoamine oxidase inhibitor (MAOI) (certain drugs for depression, psychiatric or emotional conditions, or Parkinson’s disease), or for 2 weeks after stopping the MAOI drug. If you do not know if your prescription drug contains an MAOI, ask a doctor or pharmacist before taking this product.
- if you have ever had an allergic reaction to this product or any of its ingredients

Ask a doctor before use if you have

- thyroid disease
- high blood pressure
- liver disease
- heart disease
- diabetes
- difficulty in urination due to enlargement of the prostate gland
- persistent or chronic cough such as occurs with smoking, asthma, or emphysema
- cough that occurs with too much phlegm (mucus)

Ask a doctor or pharmacist before use if you are taking the blood thinning drug warfarin.

When using this product do not exceed recommended dosage.

Stop use

Stop use and ask a doctor if

- nervousness, dizziness, or sleeplessness occur
- pain, nasal congestion or cough gets worse or lasts more than 7 days
- new symptoms occur
- fever gets worse or lasts more than 3 days
- redness or swelling is present
- cough comes back or is accompanied by a fever, rash or persistent headache. These could be signs of a serious condition.

PREGNANCY OR BREAST FEEDING

If pregnant or breast-feeding, ask a health professional before use.

Keep out of reach of children. In case of accidental overdose, get medical help or contact a Poison Control Center right away. Prompt medical attention is critical for adults as well as for children even if you do not notice any signs or symptoms.

Directions

- do not take more than directed
- adults and children 12 years and over
- take 2 caplets every 4 hours
- swallow whole - do not crush, chew or dissolve
- do not take more than 10 caplets in 24 hours
- children under 12 years: ask a doctor

Other information

- store at 25˚C (77˚F); excursions permitted between 15˚-30˚C (59˚-86˚F)
- see end flap for expiration date and lot number

Inactive ingredients

corn starch, croscarmellose sodium, crospovidone, flavor, magnesium stearate, microcrystalline cellulose, polyethylene glycol, polyvinyl alcohol, povidone, silicon dioxide, stearic acid, sucralose, talc, titanium dioxide

Questions or comments?

call toll-free 1-877-507-6516 (M-F 8AM-4:30PM CST)

Tamper evident statement

TAMPER EVIDENT: DO NOT USE IF OUTER PACKAGE IS OPENED OR BLISTER IS TORN, BROKEN OR SHOWS SIGNS OF TAMPERING

PDP/Package

TEMPORARILY RELIEVES COLD/FLU SYMPTOMS
Compare to the active ingredients in
Tylenol® Cold Max*

CIRCLE K™

non-drowsy

max cold

Acetaminophen, Dextromethorphan HBr,
Phenylephrine HCI
Pain Reliever/Fever Reducer,
Cough Suppressant,
Nasal Decongestant

[caplet image]

actual size

6 caplets